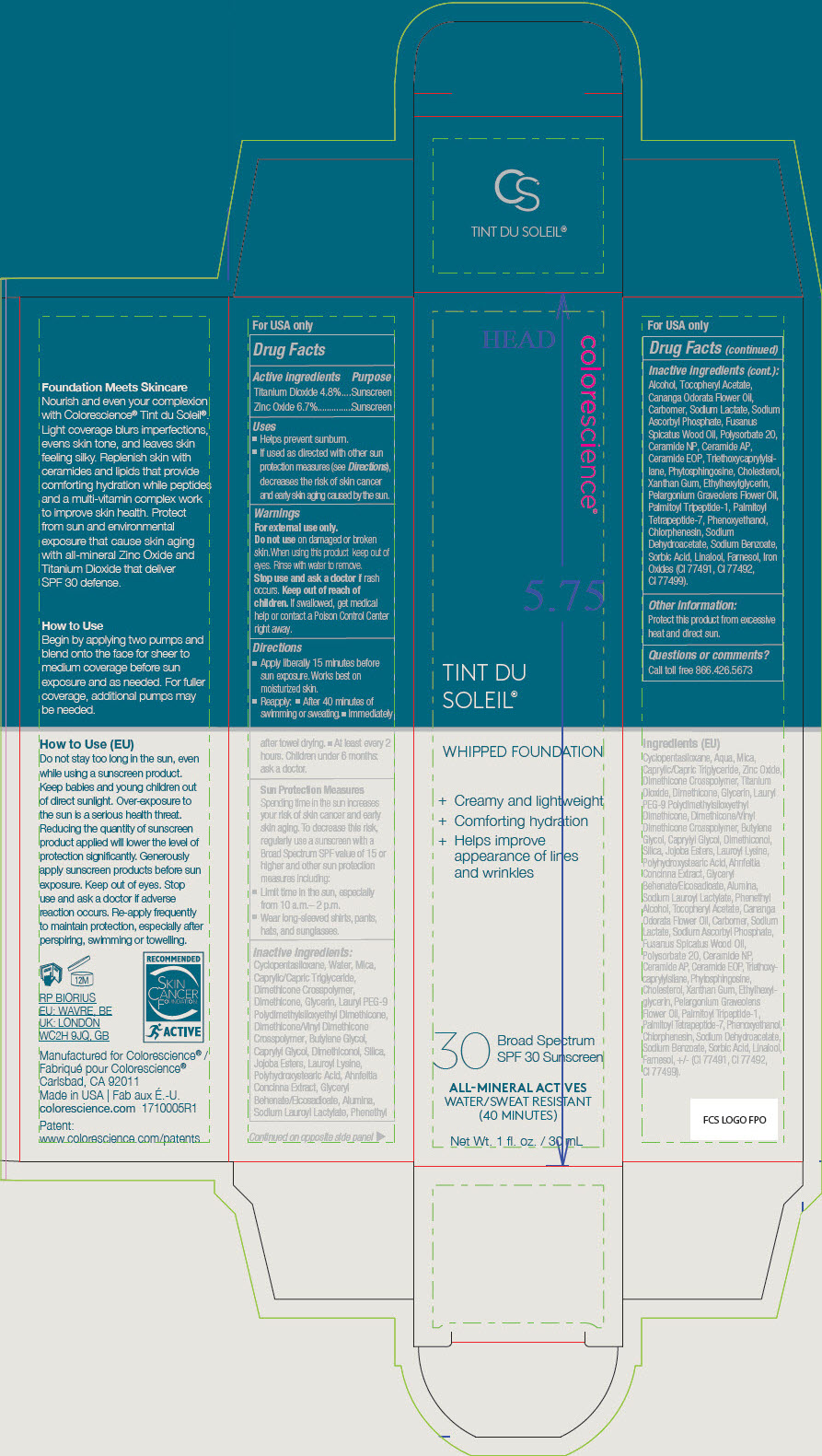 DRUG LABEL: Sunforgettable Tint du Soleil Foundation SPF 30 Sunscreen
NDC: 68078-004 | Form: LIQUID
Manufacturer: Colorescience
Category: otc | Type: HUMAN OTC DRUG LABEL
Date: 20241212

ACTIVE INGREDIENTS: Titanium Dioxide 48 mg/1 mL; Zinc Oxide 67 mg/1 mL
INACTIVE INGREDIENTS: CYCLOMETHICONE 5; MICA; DIMETHICONE/VINYL DIMETHICONE CROSSPOLYMER (SOFT PARTICLE); LAURYL PEG-9 POLYDIMETHYLSILOXYETHYL DIMETHICONE; WATER; BUTYLENE GLYCOL; CAPRYLYL GLYCOL; GLYCERIN; DIMETHICONE; SILICON DIOXIDE; LAUROYL LYSINE; TRIETHOXYCAPRYLYLSILANE; AHNFELTIOPSIS CONCINNA; SANTALUM SPICATUM OIL; GLYCERYL BEHENATE/EICOSADIOATE; ALUMINUM OXIDE; MEDIUM-CHAIN TRIGLYCERIDES; PHENOXYETHANOL; PHENYLETHYL ALCOHOL; .ALPHA.-TOCOPHEROL ACETATE; YLANG-YLANG OIL; SODIUM LACTATE; SODIUM ASCORBYL PHOSPHATE; XANTHAN GUM; CHLORPHENESIN; CERAMIDE NP; POLYSORBATE 20; SODIUM DEHYDROACETATE; SODIUM BENZOATE; Sodium Lauroyl Lactylate; Ceramide AP; CERAMIDE 1; Phytosphingosine; Pelargonium Graveolens Flower Oil; Cholesterol; Ethylhexylglycerin; LINALOOL, (+/-)-; Farnesol; SORBIC ACID; PALMITOYL TRIPEPTIDE-1; PALMITOYL TETRAPEPTIDE-7; DIMETHICONE CROSSPOLYMER (450000 MPA.S AT 12% IN CYCLOPENTASILOXANE); DIMETHICONOL (100000 CST); JOJOBA OIL; POLYHYDROXYSTEARIC ACID STEARATE; CARBOMER HOMOPOLYMER, UNSPECIFIED TYPE; FERRIC OXIDE RED; FERRIC OXIDE YELLOW; FERROSOFERRIC OXIDE

Sunforgettable® Tint du Soleil™ Foundation SPF 30 Sunscreen

Drug Facts

ACTIVE INGREDIENT

Active ingredients | Purpose
Titanium Dioxide 4.8% | Sunscreen
Zinc Oxide 6.7% | Sunscreen

Uses

- Helps prevent sunburn.
- If used as directed with other sun protection measures (see Directions), decreases the risk of skin cancer and early skin aging caused by the sun.

Warnings

For external use only.

Do not use on damaged or broken skin.When using this product keep out of eyes. Rinse with water to remove.

Stop use and ask a doctor if rash occurs.

Keep out of reach of children. If swallowed, get medical help or contact a Poison Control Center right away.

Directions

- Apply liberally 15 minutes before sun exposure. Works best on moisturized skin.
- Reapply:
  - After 40 minutes of swimming or sweating.
  - Immediately after towel drying.
  - At least every 2 hours. Children under 6 months: ask a doctor.

Sun Protection Measures

Spending time in the sun increases your risk of skin cancer and early skin aging. To decrease this risk, regularly use a sunscreen with a Broad Spectrum SPF value of 15 or higher and other sun protection measures including:

- Limit time in the sun, especially from 10 a.m.– 2 p.m.
- Wear long-sleeved shirts, pants, hats, and sunglasses.

Inactive ingredients

Cyclopentasiloxane, Water, Mica, Caprylic/Capric Triglyceride, Dimethicone Crosspolymer, Dimethicone, Glycerin, Lauryl PEG-9 Polydimethylsiloxyethyl Dimethicone, Dimethicone/Vinyl Dimethicone Crosspolymer, Butylene Glycol, Caprylyl Glycol, Dimethiconol, Silica, Jojoba Esters, Lauroyl Lysine, Polyhydroxystearic Acid, Ahnfeltia Concinna Extract, Glyceryl Behenate/Eicosadioate, Alumina, Sodium Lauroyl Lactylate, Phenethyl Alcohol, Tocopheryl Acetate, Cananga Odorata Flower Oil, Carbomer, Sodium Lactate, Sodium Ascorbyl Phosphate, Fusanus Spicatus Wood Oil, Polysorbate 20, Ceramide NP, Ceramide AP, Ceramide EOP, Triethoxycaprylylsilane, Phytosphingosine, Cholesterol, Xanthan Gum, Ethylhexylglycerin, Pelargonium Graveolens Flower Oil, Palmitoyl Tripeptide-1, Palmitoyl Tetrapeptide-7, Phenoxyethanol, Chlorphenesin, Sodium Dehydroacetate, Sodium Benzoate, Sorbic Acid, Linalool, Farnesol, Iron Oxides (CI 77491, CI 77492, CI 77499).

Other information

Protect this product from excessive heat and direct sun.

Questions or comments?

Call toll free 866.426.5673

PRINCIPAL DISPLAY PANEL - 30 mL Tube Carton

colorescience®

TINT DU
SOLEIL®

WHIPPED FOUNDATION

+ Creamy and lightweight
+ Comforting hydration
+ Helps improve
  appearance of lines
  and wrinkles

30
Broad Spectrum
SPF 30 Sunscreen

ALL-MINERAL ACTIVES
WATER/SWEAT RESISTANT
(40 MINUTES)

Net Wt. 1 fl. oz. / 30 mL